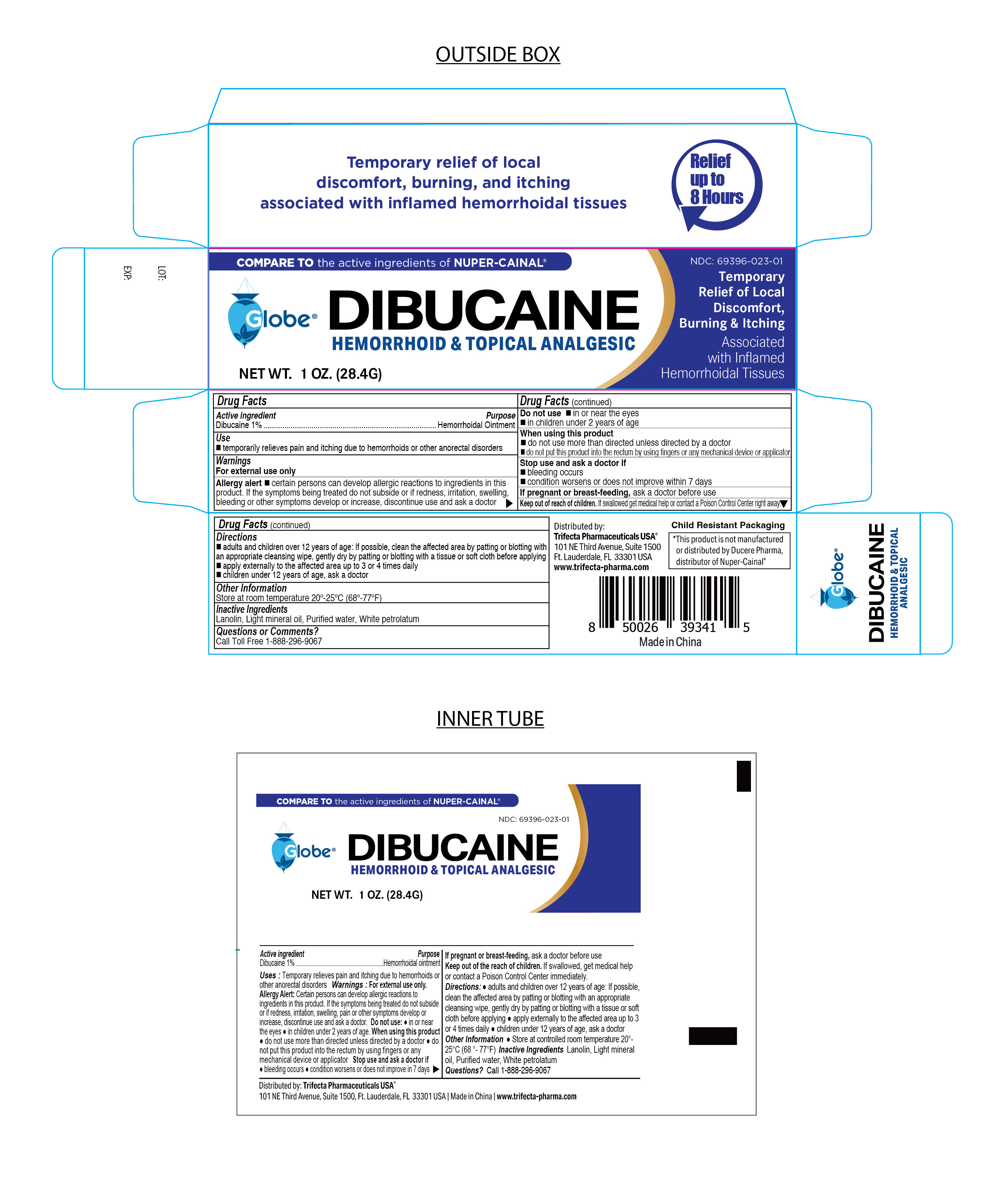 DRUG LABEL: Dibucaine
NDC: 69396-023 | Form: OINTMENT
Manufacturer: Trifecta Pharmaceuticals USA LLC
Category: otc | Type: HUMAN OTC DRUG LABEL
Date: 20240102

ACTIVE INGREDIENTS: DIBUCAINE 1 g/100 g
INACTIVE INGREDIENTS: PETROLATUM; WATER; LIGHT MINERAL OIL; LANOLIN

Globe Dibucaine Ointment 1%

Active Ingredient

Dibucaine 1%

PURPOSE

Hemorrhoidal Ointment

INDICATIONS AND USAGE

Temporarily relieves pain and itching due to hemorrhoids or other anorectal disorders.

If Pregnant or Breast-Feeding

Ask a health care professional before use.

Stop Use and ask a doctor

- Bleeding occurs
- Condition worsens or does not improve within 7 days

Keep out of the reach of Children

If swallowed, get medical help or contact a Poison Control Center right away.

Do Not Use

In or near eyes

In children under 2 years of age

Warnings

For External use only

Allergy alert

Certain persons can develop allergic reactions to ingredients in this product.

If the symptoms being treated do not subside or if redness, irritation, swelling, bleeding or other symptoms develop or increase, discontinue use and ask a doctor.

When using this product

Do not use more than directed unless directed by a doctor

Do not put this product into the rectum by using fingers or any mechanical device or applicator.

Directions

- Adults and children 12 years of age or older. If possible, clean the affected area by platting or blotting with an appropriate cleansing wipe, gently dry by patting or blotting with a tissue or a soft cloth before applying.
- Apply externally to the affected area up to 3 to 4 times daily.

Children under 12 years of age. ask a doctor

Questions or Comments?

Call Toll Free 1-888-296-9067

Other Information

- Store at room temperature 20º-25ºC (68º-77ºF)

Inactive Ingredients

Lanolin, Light Mineral Oil, Purified Water, White Petrolatum

Distributed By

Trifecta Pharmaceuticals USA

101 NE Third Avenue, Suite 1500

Ft. Lauderdale, FL. 33301 USA

1-888-296-9067

Made in China

* This product is not manufactured or distributed by Ducere Pharma, Distributor of Nuper-Cainal

Child Resistant Packaging